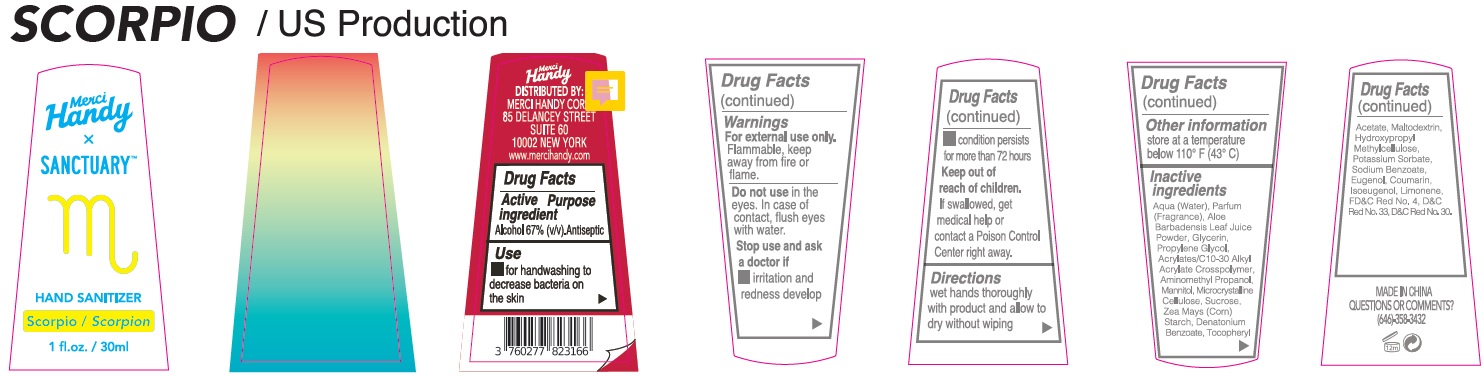 DRUG LABEL: Merci Handy Sanctuary Hand Sanitizer SCORPIO
NDC: 72866-025 | Form: GEL
Manufacturer: MERCI HANDY CORPORATION
Category: otc | Type: HUMAN OTC DRUG LABEL
Date: 20221201

ACTIVE INGREDIENTS: ALCOHOL 67 mL/100 mL
INACTIVE INGREDIENTS: WATER; ALOE VERA LEAF; GLYCERIN; PROPYLENE GLYCOL; CARBOMER INTERPOLYMER TYPE A (ALLYL SUCROSE CROSSLINKED); AMINOMETHYLPROPANOL; MANNITOL; MICROCRYSTALLINE CELLULOSE; SUCROSE; CORN; DENATONIUM BENZOATE; .ALPHA.-TOCOPHEROL ACETATE; MALTODEXTRIN; HYPROMELLOSE, UNSPECIFIED; POTASSIUM SORBATE; SODIUM BENZOATE; EUGENOL; COUMARIN; ISOEUGENOL; LIMONENE, (+)-; FD&C RED NO. 4; D&C RED NO. 33; D&C RED NO. 30

Merci Handy Sanctuary Hand Sanitizer SCORPIO

Active ingredient

Alcohol 67% (v/v)

Purpose

Antiseptic

Use

- for handwashing to decrease bacteria on the skin

Warnings

For external use only.

Flammable, keep away from fire or flame.

Do not use

in the eyes. In the case of contact, flush eyes with water.

Stop use and ask a doctor if

- irritation and redness develop
- condition persists for more than 72 hours

Keep out of reach of children.

If swallowed, get medical help or contact a Poison Control Center right away

Directions

wet hands thoroughly with product and allow to dry without wiping

Other information

store at a temperature below 110° F (43° C)

Inactive Ingredients

Aqua (Water), Parfum (Fragrance), Aloe Barbadensis Leaf Juice Powder, Glycerin, Propylene Glycol, Acrylates/C10-30 Alkyl Acrylate Crosspolymer, Aminomethyl Propanol, Mannitol, Microcrystalline Cellulose, Sucrose, Zea Mays (Corn) Starch, Denatonium Benzoate, Tocopheryl Acetate, Maltodextrin, Hydroxypropyl Methylcellulose, Potassium Sorbate, Sodium Benzoate, Eugenol, Coumarin, Isoeugenol, Limonene, FD&C Red No. 4, D&C Red No. 33, D&C Red No. 30.

QUESTIONS OR COMMENTS?

(646)-358-3432